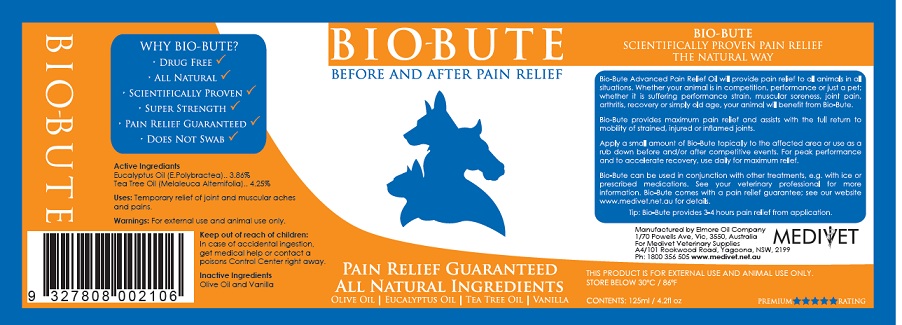 DRUG LABEL: Bio Bute
NDC: 51083-100 | Form: OIL
Manufacturer: Medivet Pty Ltd
Category: animal | Type: OTC ANIMAL DRUG LABEL
Date: 20120907

ACTIVE INGREDIENTS: TEA TREE OIL 42.5 mg/1 mL; EUCALYPTUS OIL 38.6 mg/1 mL
INACTIVE INGREDIENTS: Olive Oil

Active ingredient

ACTIVE INGREDIENT

Tea Tree Oil (Melaleuca Alternifolia) - 4.25% (42.5 mg/ml)
Eucalyptus Oil (E. Polybractea) - 3.86% (38.6 mg/ml)

Uses

Massage Oil to assist with relief of joint and muscle pain

Warnings

For External and Animal Use Only

Keep Out of Reach of Children. In case of accidental ingestion, get medical help or contact a Poisons Control Center right away

Inactive Ingredient Section

Olive Oil (INCI name: Olea Europaea (Olive) Oil)
Vanilla (INCI Name: Vanillin)

Package Label Principal Display Panel

For Animal Use Only
Store below 30 degrees C / 86 degrees F
Manufactured By Elmore Oil Company
1/70 Powells Av, VIC 3550 Australia.
For Medivet Veterinary Supplies
A4/101 Rookwood Road. Yagoan NSW 2199